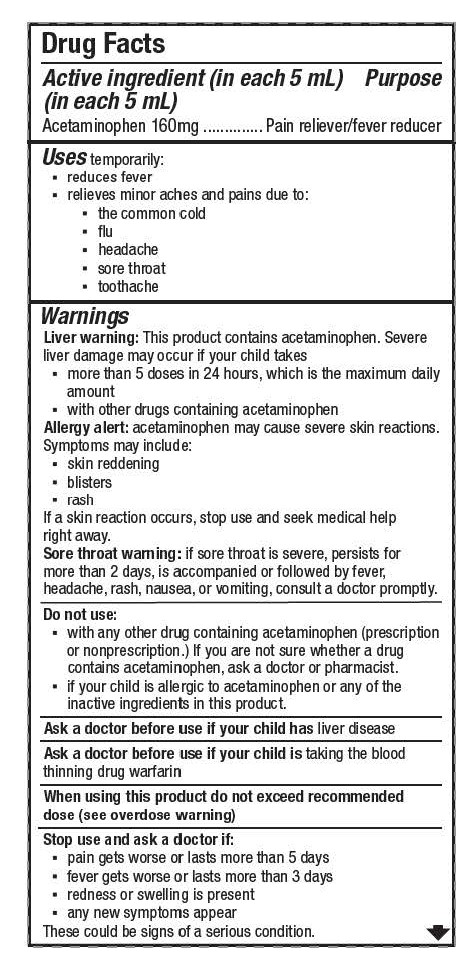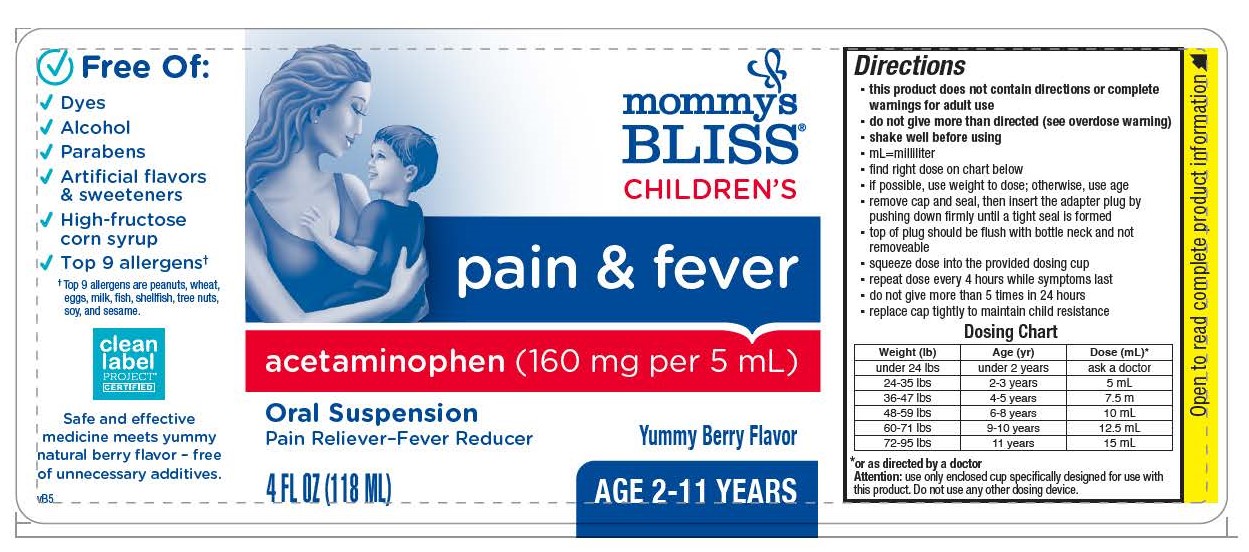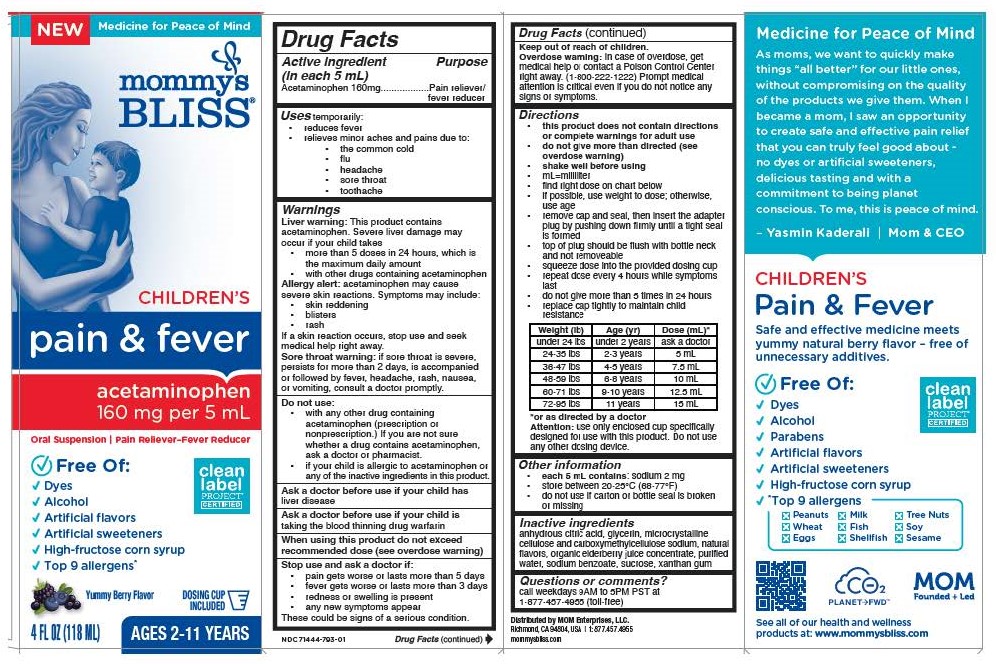 DRUG LABEL: Mommys Bliss Childrens Pain and Fever
NDC: 71444-793 | Form: SUSPENSION
Manufacturer: Mom Enterprises, LLC.
Category: otc | Type: HUMAN OTC DRUG LABEL
Date: 20240412

ACTIVE INGREDIENTS: ACETAMINOPHEN 160 mg/5 mL
INACTIVE INGREDIENTS: SODIUM BENZOATE; GLYCERIN; CARBOXYMETHYLCELLULOSE SODIUM; WATER; ANHYDROUS CITRIC ACID; SUCROSE; XANTHAN GUM; AMERICAN ELDERBERRY

Mommys Bliss Childrens Pain and Fever

Inactive ingredients:

anhydrous citric acid, glycerin, microcrystalline cellulose and carboxymethylcellulose sodium, natural flavors, organic elderberry juice concentrate, purified water, sodium benzoate, sucrose, xanthan gum

USE:

Purpose: Pain reliever/fever reducer

Uses temporarily:
▪ reduces fever
▪ relieves minor aches and pains due to:
▪ the common cold
▪ flu
▪ headache
▪ sore throat
▪ toothache

Directions and Dosing:

Directions
▪ this product does not contain directions or complete warnings for adult use
▪ do not give more than directed (see overdose warning)
▪ shake well before using
▪ mL=milliliter
▪ find right dose on chart below
▪ if possible, use weight to dose; otherwise, use age
▪ remove cap and seal, then insert the adapter plug by pushing down firmly until a tight seal is formed
▪ top of plug should be flush with bottle neck and not removeable
▪ squeeze dose into the provided dosing cup
▪ repeat dose every 4 hours while symptoms last
▪ do not give more than 5 times in 24 hours
▪ replace cap tightly to maintain child resistance

Dosing:

Weight (lb) Age (yr) Dose (mL)*
under 24 lbs under 2 years ask a doctor
24-35 lbs 2-3 years 5 mL
36-47 lbs 4-5 years 7.5 mL
48-59 lbs 6-8 years 10 mL
60-71 lbs 9-10 years 12.5 mL
72-95 lbs 11 years 15 mL
*or as directed by a doctor

Attention: use only enclosed cup specifically designed for use with this product. Do not use any other dosing device.

Warnings:

Liver warning: This product contains acetaminophen. Severe liver damage may occur if your child takes
▪ more than 5 doses in 24 hours, which is the maximum daily amount
▪ with other drugs containing acetaminophen
Allergy alert: acetaminophen may cause severe skin reactions. Symptoms may include:
▪ skin reddening
▪ blisters
▪ rash
If a skin reaction occurs, stop use and seek medical help right away.
Sore throat warning: if sore throat is severe, persists for more than 2 days, is accompanied or followed by fever, headache, rash, nausea, or vomiting, consult a doctor promptly.
Do not use:
▪ with any other drug containing acetaminophen (prescription or nonprescription.) If you are not sure whether a drug contains acetaminophen, ask a doctor or pharmacist.
▪ if your child is allergic to acetaminophen or any of the inactive ingredients in this product.

Ask a doctor before use if your child has liver disease

Ask a doctor before use if your child is taking the blood thinning drug warfarin

When using this product do not exceed recommended dose (see overdose warning)

Stop use and ask a doctor if:
▪ pain gets worse or lasts more than 5 days
▪ fever gets worse or lasts more than 3 days
▪ redness or swelling is present
▪ any new symptoms appear
These could be signs of a serious condition.

Keep out of reach of children.

Overdose warning: In case of overdose, get medical help or contact a Poison Control Center right away. (1-800-222-1222) Prompt medical
attention is critical even if you do not notice any signs or symptoms.

Active ingredient:

Active ingredient: (in each 5 mL) Acetaminophen 160mg

WARNINGS:

Liver warning: This product contains acetaminophen. Severe liver damage may occur if your child takes
▪ more than 5 doses in 24 hours, which is the maximum daily amount
▪ with other drugs containing acetaminophen

Allergy alert: acetaminophen may cause severe skin reactions. Symptoms may include:
▪ skin reddening
▪ blisters
▪ rash
If a skin reaction occurs, stop use and seek medical help right away.

Sore throat warning: if sore throat is severe, persists for more than 2 days, is accompanied or followed by fever, headache, rash, nausea, or vomiting, consult a doctor promptly.

Do not use:
▪ with any other drug containing acetaminophen (prescription or nonprescription.) If you are not sure whether a drug contains acetaminophen, ask a doctor or pharmacist.
▪ if your child is allergic to acetaminophen or any of the inactive ingredients in this product.

Ask a doctor before use if your child has liver disease

Ask a doctor before use if your child is taking the blood thinning drug warfarin

When using this product do not exceed recommended dose (see overdose warning)

Stop use and ask a doctor if:
▪ pain gets worse or lasts more than 5 days
▪ fever gets worse or lasts more than 3 days
▪ redness or swelling is present
▪ any new symptoms appear
These could be signs of a serious condition.

Keep out of reach of children.

Overdose warning:

In case of overdose, get medical help or contact a Poison Control Center right away. (1-800-222-1222) Prompt medical
attention is critical even if you do not notice any signs or symptoms.

Keep out of reach of Children.

Overdose warning:

In case of overdose, get medical help or contact a Poison Control Center right away. (1-800-222-1222)

Prompt medical attention is critical even if you do not notice any signs or symptoms.

Purpose and Use:

Purpose:

Pain reliever/fever reducer

Uses temporarily:
▪ reduces fever
▪ relieves minor aches and pains due to:
▪ the common cold
▪ flu
▪ headache
▪ sore throat
▪ toothache

Children's Pain and Fever Acetaminophen 160mg per 5mL oral suspension

Pain Reliever - Fever Reducer, 4 floz (118 mL) bottle in carton, Ages 2-11 years, Berry Flavor, Dosing Cup Included